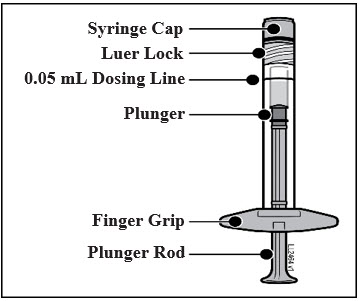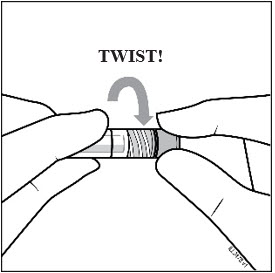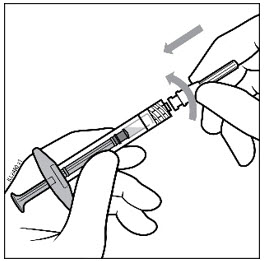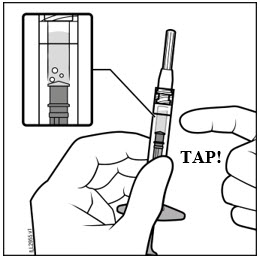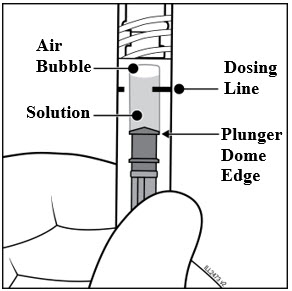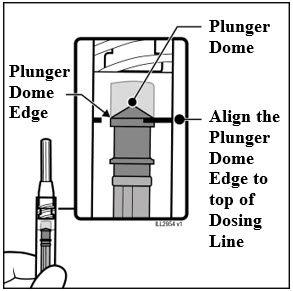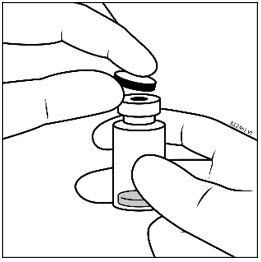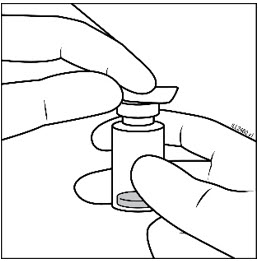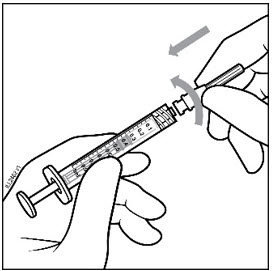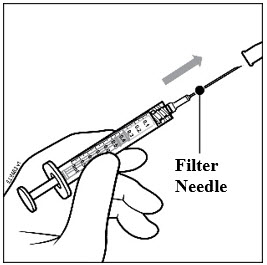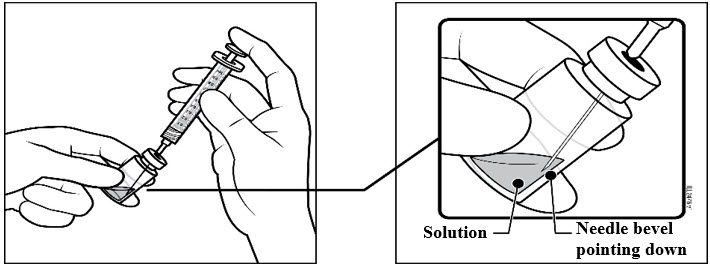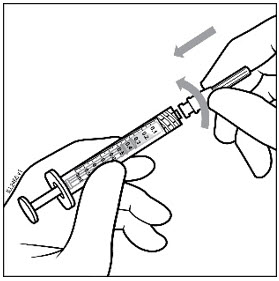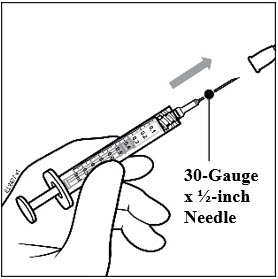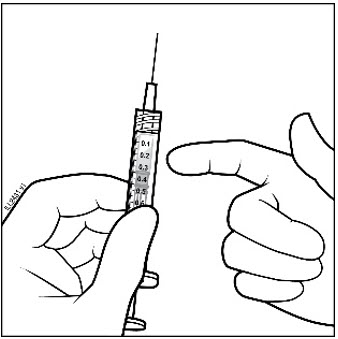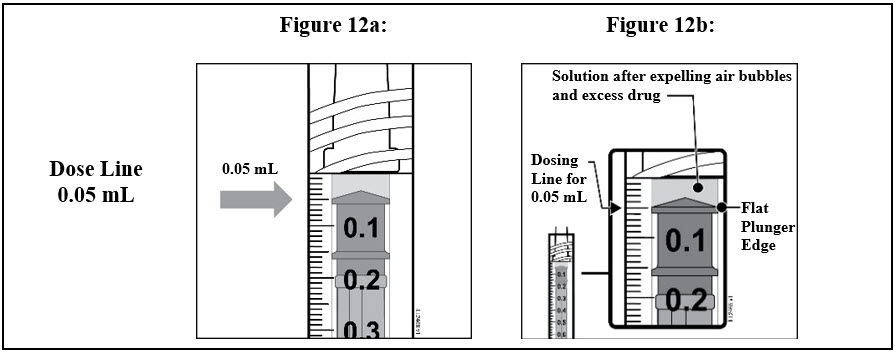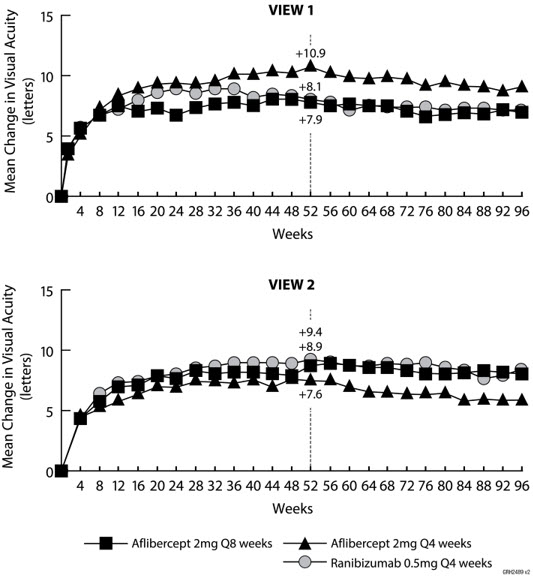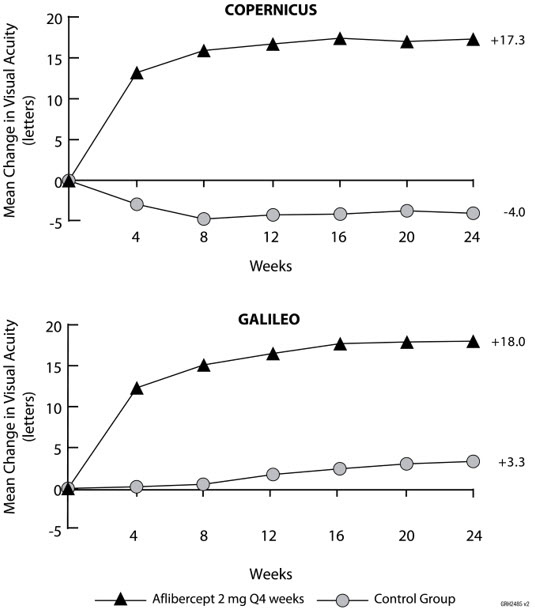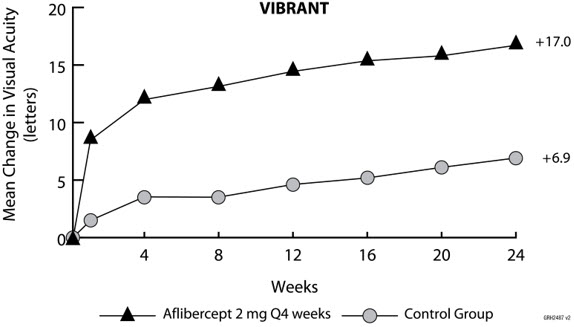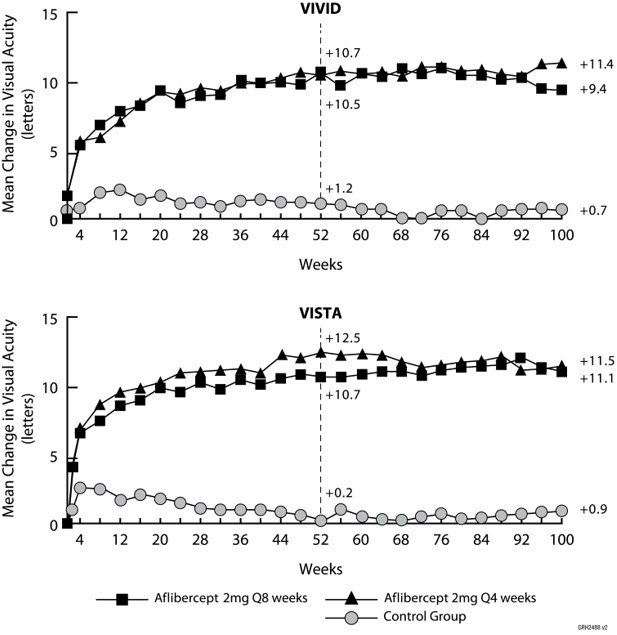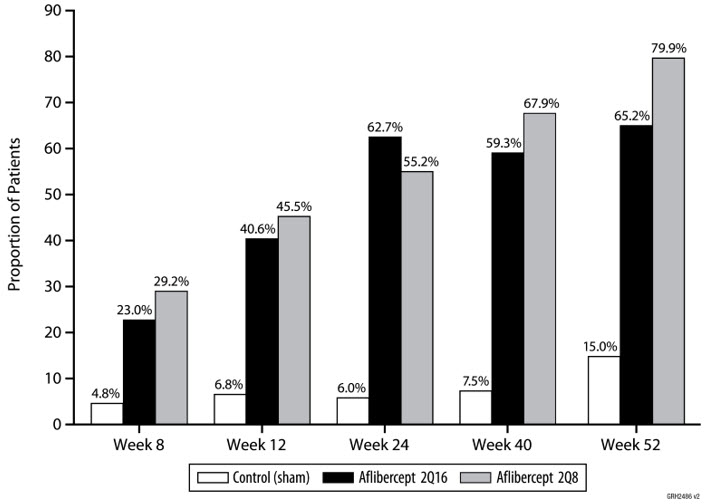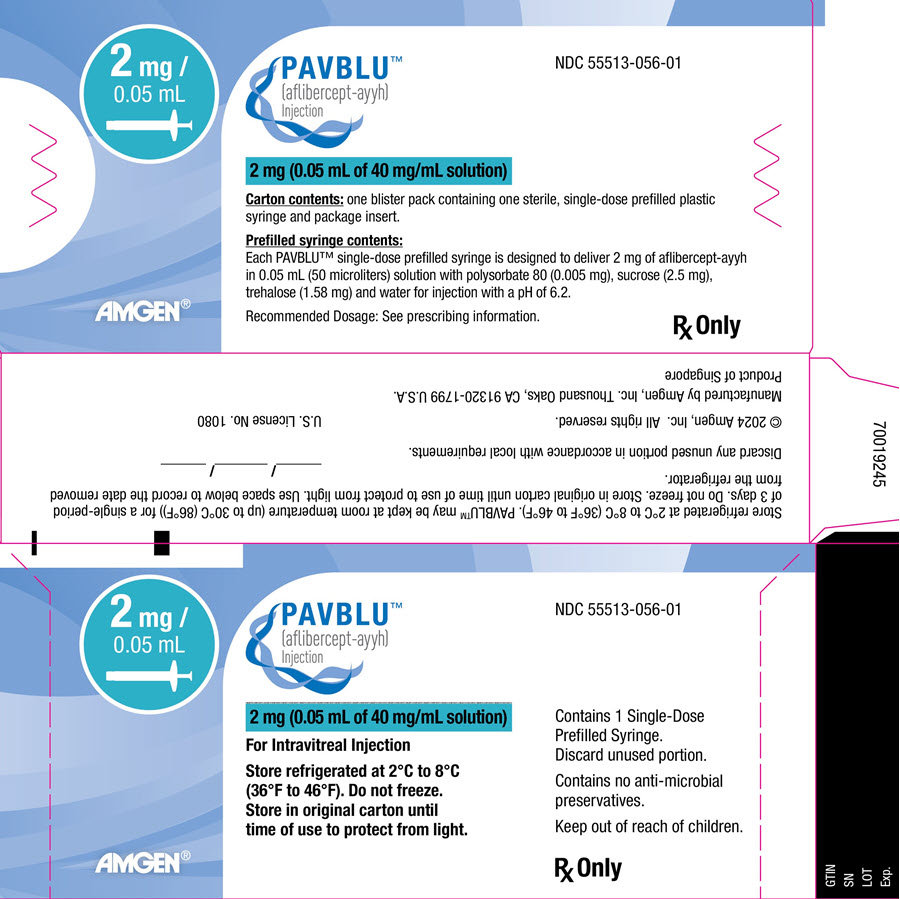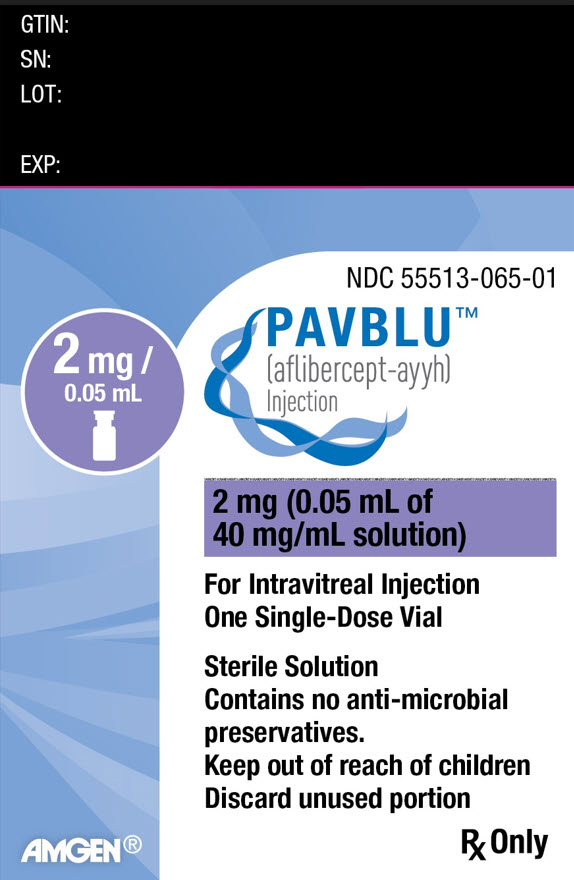 DRUG LABEL: PAVBLU
NDC: 55513-056 | Form: INJECTION, SOLUTION
Manufacturer: Amgen, Inc
Category: prescription | Type: HUMAN PRESCRIPTION DRUG LABEL
Date: 20250304

ACTIVE INGREDIENTS: AFLIBERCEPT 2 mg/0.05 mL
INACTIVE INGREDIENTS: TREHALOSE DIHYDRATE; POLYSORBATE 80; SUCROSE

HIGHLIGHTS OF PRESCRIBING INFORMATION

These highlights do not include all the information needed to use PAVBLU safely and effectively. See full prescribing information for PAVBLU.
PAVBLU™ (aflibercept-ayyh) injection, for intravitreal use
Initial U.S. Approval: 2024
PAVBLU (aflibercept-ayyh) is biosimilar [Biosimilar means that the biological product is approved based on data demonstrating that it is highly similar to an FDA-approved biological product known as a reference product, and that there are no clinically meaningful differences between the biosimilar product and the reference product. Biosimilarity of PAVBLU has been demonstrated for the condition(s) of use (e.g., indication(s), dosing regimen(s), strength(s), dosage form(s), and route(s) of administration described in its Full Prescribing Information.] to EYLEA® (aflibercept).

1 INDICATIONS AND USAGE

PAVBLU is a vascular endothelial growth factor (VEGF) inhibitor indicated for the treatment of patients with:

- Neovascular (Wet) Age-Related Macular Degeneration (AMD) (1.1)
- Macular Edema Following Retinal Vein Occlusion (RVO) (1.2)
- Diabetic Macular Edema (DME) (1.3)
- Diabetic Retinopathy (DR) (1.4)

2 DOSAGE AND ADMINISTRATION

Neovascular (Wet) Age-Related Macular Degeneration (AMD):

- The recommended dose for PAVBLU is 2 mg (0.05 mL of 40 mg/mL solution) administered by intravitreal injection every 4 weeks (approximately every 28 days, monthly) for the first 3 months, followed by 2 mg (0.05 mL of 40 mg/mL solution) via intravitreal injection once every 8 weeks (2 months). (2.2)
- Although PAVBLU may be dosed as frequently as 2 mg every 4 weeks (approximately every 25 days, monthly), additional efficacy was not demonstrated in most patients when aflibercept was dosed every 4 weeks compared to every 8 weeks. Some patients may need every 4 week (monthly) dosing after the first 12 weeks (3 months). (2.2)
- Although not as effective as the recommended every 8 week dosing regimen, patients may also be treated with one dose every 12 weeks after one year of effective therapy. Patients should be assessed regularly. (2.2)

Macular Edema Following Retinal Vein Occlusion (RVO):

- The recommended dose for PAVBLU is 2 mg (0.05 mL of 40 mg/mL solution) administered by intravitreal injection once every 4 weeks (approximately every 25 days, monthly). (2.3)

Diabetic Macular Edema (DME) and Diabetic Retinopathy (DR):

- The recommended dose for PAVBLU is 2 mg (0.05 mL of 40 mg/mL solution) administered by intravitreal injection every 4 weeks (approximately every 28 days, monthly) for the first 5 injections followed by 2 mg (0.05 mL of 40 mg/mL solution) via intravitreal injection once every 8 weeks (2 months). (2.4, 2.5)
- Although PAVBLU may be dosed as frequently as 2 mg every 4 weeks (approximately every 25 days, monthly), additional efficacy was not demonstrated in most patients when aflibercept was dosed every 4 weeks compared to every 8 weeks. Some patients may need every 4 week (monthly) dosing after the first 20 weeks (5 months). (2.4, 2.5)

3 DOSAGE FORMS AND STRENGTHS

- Injection: 2 mg (0.05 mL of 40 mg/mL) solution in a single-dose prefilled syringe (3)
- Injection: 2 mg (0.05 mL of 40 mg/mL) solution in a single-dose vial (3)

4 CONTRAINDICATIONS

- Ocular or periocular infections (4.1)
- Active intraocular inflammation (4.2)
- Hypersensitivity (4.3)

5 WARNINGS AND PRECAUTIONS

- Endophthalmitis, retinal detachments, and retinal vasculitis with or without occlusion may occur following intravitreal injections. Patients and/or caregivers should be instructed to report any signs and/or symptoms suggestive of endophthalmitis, retinal detachment, or retinal vasculitis without delay and should be managed appropriately. (5.1)
- Increases in intraocular pressure have been seen within 60 minutes of an intravitreal injection. (5.2)
- There is a potential risk of arterial thromboembolic events following intravitreal use of VEGF inhibitors. (5.4)

6. ADVERSE REACTIONS

The most common adverse reactions (≥5%) reported in patients receiving aflibercept were conjunctival hemorrhage, eye pain, cataract, vitreous detachment, vitreous floaters, and intraocular pressure increased. (6.1)

To report SUSPECTED ADVERSE REACTIONS, contact Amgen Inc. at 1-800-77-AMGEN (1-800-772-6436) or FDA at 1-800-FDA-1088 or www.fda.gov/medwatch.

FULL PRESCRIBING INFORMATION

1 INDICATIONS AND USAGE

PAVBLU is indicated for the treatment of:

2 DOSAGE AND ADMINISTRATION

2.1 Important Injection Instructions

For ophthalmic intravitreal injection. PAVBLU must only be administered by a qualified physician.

Prefilled Syringe: A 30-gauge × ½-inch sterile injection needle is needed but not provided.

Vial: A 5-micron sterile filter needle (18-gauge × 1½-inch), a 1-mL Luer lock syringe and a 30-gauge × ½-inch sterile injection needle are needed but not provided.

PAVBLU is available packaged as follows:

- Prefilled Syringe
- Vial Only

[see How Supplied/Storage and Handling (16)].

2.2 Neovascular (Wet) Age-Related Macular Degeneration (AMD)

The recommended dose for PAVBLU is 2 mg (0.05 mL of 40 mg/mL solution) administered by intravitreal injection every 4 weeks (approximately every 28 days, monthly) for the first 12 weeks (3 months), followed by 2 mg (0.05 mL of 40 mg/mL solution) via intravitreal injection once every 8 weeks (2 months). Although PAVBLU may be dosed as frequently as 2 mg every 4 weeks (approximately every 25 days, monthly), additional efficacy was not demonstrated in most patients when aflibercept was dosed every 4 weeks compared to every 8 weeks [see Clinical Studies (14.1)]. Some patients may need every 4 week (monthly) dosing after the first 12 weeks (3 months). Although not as effective as the recommended every 8 week dosing regimen, patients may also be treated with one dose every 12 weeks after one year of effective therapy. Patients should be assessed regularly.

2.3 Macular Edema Following Retinal Vein Occlusion (RVO)

The recommended dose for PAVBLU is 2 mg (0.05 mL of 40 mg/mL solution) administered by intravitreal injection once every 4 weeks (approximately every 25 days, monthly) [see Clinical Studies (14.2), (14.3)].

2.4 Diabetic Macular Edema (DME)

The recommended dose for PAVBLU is 2 mg (0.05 mL of 40 mg/mL solution) administered by intravitreal injection every 4 weeks (approximately every 28 days, monthly) for the first 5 injections, followed by 2 mg (0.05 mL of 40 mg/mL solution) via intravitreal injection once every 8 weeks (2 months). Although PAVBLU may be dosed as frequently as 2 mg every 4 weeks (approximately every 25 days, monthly), additional efficacy was not demonstrated in most patients when aflibercept was dosed every 4 weeks compared to every 8 weeks [see Clinical Studies (14.4)]. Some patients may need every 4 week (monthly) dosing after the first 20 weeks (5 months).

2.5 Diabetic Retinopathy (DR)

The recommended dose for PAVBLU is 2 mg (0.05 mL of 40 mg/mL solution) administered by intravitreal injection every 4 weeks (approximately every 28 days, monthly) for the first 5 injections, followed by 2 mg (0.05 mL of 40 mg/mL solution) via intravitreal injection once every 8 weeks (2 months). Although PAVBLU may be dosed as frequently as 2 mg every 4 weeks (approximately every 25 days, monthly), additional efficacy was not demonstrated in most patients when aflibercept was dosed every 4 weeks compared to every 8 weeks [see Clinical Studies (14.5)]. Some patients may need every 4 week (monthly) dosing after the first 20 weeks (5 months).

2.6 Preparation for Administration - Prefilled Syringe

The PAVBLU prefilled plastic syringe is sterile and for one-time use in one eye only.

The prefilled syringe should be inspected visually prior to administration. It is a clear to opalescent and colorless to slightly yellow solution. Do not use if particulates, cloudiness, or discoloration are visible, or if the package is open or damaged. The appearance of the syringe cap on the prefilled syringe may vary (for example, color and design).

Do not use if any part of the prefilled syringe is damaged or if the syringe cap is detached from the Luer lock.

The intravitreal injection should be performed with a 30-gauge × ½-inch injection needle (not provided).

The prefilled syringe contains more than the recommended dose of 2 mg aflibercept-ayyh (equivalent to 50 microliters). The excess volume must be discarded prior to the administration.

PREFILLED SYRINGE DESCRIPTION - Figure 1:

Use aseptic technique to carry out the following steps:

1. PREPARE

When ready to administer PAVBLU, open the carton and remove sterilized blister pack. Carefully peel open the sterilized blister pack ensuring the sterility of its contents. Keep the syringe in the sterile tray until you are ready for assembly.

2. REMOVE SYRINGE

Using aseptic technique, remove the syringe from the sterilized blister pack.

3. TWIST OFF SYRINGE CAP

Twist off (do not snap off) the syringe cap by holding the syringe in one hand and the syringe cap with the thumb and forefinger of the other hand (see Figure 2).

Figure 2:

4. ATTACH NEEDLE

Using aseptic technique, firmly twist a 30-gauge × ½-inch injection needle onto the Luer lock syringe tip (see Figure 3).

Figure 3:

Note: When ready to administer PAVBLU, remove the plastic needle shield from the needle.

5. DISLODGE AIR BUBBLES

Holding the syringe with the needle pointing up, check the syringe for bubbles. If there are bubbles, gently tap the syringe with your finger until the bubbles rise to the top (see Figure 4).

Figure 4:

6. EXPEL AIR AND SET THE DOSE

To eliminate all bubbles and to expel excess drug, slowly depress the plunger rod to align the plunger dome edge (see Figure 5a) with the black dosing line on the syringe (equivalent to 50 microliters) (see Figure 5b).

Figure 5a:

Figure 5b:

7. The prefilled syringe is for one-time use in one eye only. After injection any unused product must be discarded.

2.7 Preparation for Administration - Vial

PAVBLU should be inspected visually prior to administration. It is a clear to opalescent and colorless to slightly yellow solution. If particulates, cloudiness, or discoloration are visible, the vial must not be used.

The glass vial is for one-time use in one eye only.

Use aseptic technique to carry out the following preparation steps:

Prepare for intravitreal injection with the following medical devices for single use:

- a 5-micron sterile filter needle 18-gauge × 1½-inch (not provided)
- a 1-mL sterile Luer lock syringe with marking to measure 0.05 mL (not provided)
- a sterile injection needle 30-gauge × ½-inch (not provided)

1. Remove the protective plastic cap from the vial (see Figure 6).

Figure 6:

2. Clean the top of the vial with an alcohol wipe (see Figure 7).

Figure 7:

3. Remove the 18-gauge × 1½-inch, 5-micron, filter needle and the 1-mL syringe from their packaging. Attach the filter needle to the syringe by twisting it onto the Luer lock syringe tip (see Figure 8a and Figure 8b).

Figure 8a:

Figure 8b:

Note: When ready to withdraw PAVBLU, remove the plastic needle shield from the needle.

4. Push the filter needle into the center of the vial stopper until the needle is completely inserted into the vial and the tip touches the bottom or bottom edge of the vial.
5. Using aseptic technique withdraw all of the PAVBLU vial contents into the syringe, keeping the vial in an upright position, slightly inclined to ease complete withdrawal. To deter the introduction of air, ensure the bevel of the filter needle is submerged into the liquid. Continue to tilt the vial during withdrawal keeping the bevel of the filter needle submerged in the liquid (see Figure 9a and Figure 9b).

Figure 9a: Figure 9b:

6. Ensure that the plunger rod is drawn sufficiently back when emptying the vial in order to completely empty the filter needle.
7. Remove the filter needle from the syringe and properly dispose of the filter needle. Note: Filter needle is not to be used for intravitreal injection.
8. Remove the 30-gauge × ½-inch injection needle from its packaging and attach the injection needle to the syringe by firmly twisting the injection needle onto the Luer lock syringe tip (see Figure 10a and Figure 10b).

Figure 10a:

Figure 10b:

Note: When ready to administer PAVBLU, remove the plastic needle shield from the needle.

9. Holding the syringe with the needle pointing up, check the syringe for bubbles. If there are bubbles, gently tap the syringe with your finger until the bubbles rise to the top (see Figure 11).

Figure 11:

10. To eliminate all of the bubbles and to expel excess drug, SLOWLY depress the plunger rod so that the plunger edge aligns with the line that marks 0.05 mL on the syringe (see Figure 12a and Figure 12b).

2.8 Injection Procedure

The intravitreal injection procedure should be carried out under controlled aseptic conditions, which include surgical hand disinfection and the use of sterile gloves, a sterile drape, and a sterile eyelid speculum (or equivalent). Adequate anesthesia and a topical broad−spectrum microbicide should be given prior to the injection.

Prefilled syringe: Inject by pressing the plunger carefully and with constant pressure. Do not apply additional pressure once the plunger has reached the bottom of the syringe. A small residual volume may remain in the syringe after a full dose has been injected. This is normal. Do not administer any residual solution observed in the syringe.

Immediately following the intravitreal injection, patients should be monitored for elevation in intraocular pressure. Appropriate monitoring may consist of a check for perfusion of the optic nerve head or tonometry. If required, a sterile paracentesis needle should be available.

Following intravitreal injection, patients and/or caregivers should be instructed to report any signs and/or symptoms suggestive of endophthalmitis or retinal detachment (e.g., eye pain, redness of the eye, photophobia, blurring of vision) without delay [see Patient Counseling Information (17)].

Each sterile, prefilled syringe or vial should only be used for the treatment of a single eye. If the contralateral eye requires treatment, a new sterile, prefilled syringe or vial should be used and the sterile field, syringe, gloves, drapes, eyelid speculum, filter, and injection needles should be changed before PAVBLU is administered to the other eye.

After injection, any unused product must be discarded.

3 DOSAGE FORMS AND STRENGTHS

PAVBLU is a clear to opalescent and colorless to slightly yellow solution available as:

- Injection: 2 mg (0.05 mL of 40 mg/mL solution) in a single-dose prefilled plastic syringe
- Injection: 2 mg (0.05 mL of 40 mg/mL solution) in a single-dose glass vial

4 CONTRAINDICATIONS

4.1 Ocular or Periocular Infections

PAVBLU is contraindicated in patients with ocular or periocular infections.

4.2 Active Intraocular Inflammation

PAVBLU is contraindicated in patients with active intraocular inflammation.

4.3 Hypersensitivity

PAVBLU is contraindicated in patients with known hypersensitivity to aflibercept or any of the excipients in PAVBLU. Hypersensitivity reactions may manifest as rash, pruritus, urticaria, severe anaphylactic/anaphylactoid reactions, or severe intraocular inflammation.

5 WARNINGS AND PRECAUTIONS

5.1 Endophthalmitis, Retinal Detachments, and Retinal Vasculitis with or without Occlusion

Intravitreal injections, including those with aflibercept products, have been associated with endophthalmitis and retinal detachments [see Adverse Reactions (6.1)] and, more rarely, retinal vasculitis with or without occlusion [see Adverse Reactions (6.2)]. Proper aseptic injection technique must always be used when administering PAVBLU. Patients and/or caregivers should be instructed to report any signs and/or symptoms suggestive of endophthalmitis, retinal detachment, or retinal vasculitis without delay and should be managed appropriately [see Dosage and Administration (2.8) and Patient Counseling Information (17)].

5.2 Increase in Intraocular Pressure

Acute increases in intraocular pressure have been seen within 60 minutes of intravitreal injection, including with aflibercept products [see Adverse Reactions (6.1)]. Sustained increases in intraocular pressure have also been reported after repeated intravitreal dosing with vascular endothelial growth factor (VEGF) inhibitors. Intraocular pressure and the perfusion of the optic nerve head should be monitored and managed appropriately [see Dosage and Administration (2.8)].

5.4 Thromboembolic Events

There is a potential risk of arterial thromboembolic events (ATEs) following intravitreal use of VEGF inhibitors, including aflibercept products. ATEs are defined as nonfatal stroke, nonfatal myocardial infarction, or vascular death (including deaths of unknown cause). The incidence of reported thromboembolic events in wet AMD studies during the first year was 1.8% (32 out of 1824) in the combined group of patients treated with aflibercept compared with 1.5% (9 out of 595) in patients treated with ranibizumab; through 96 weeks, the incidence was 3.3% (60 out of 1824) in the aflibercept group compared with 3.2% (19 out of 595) in the ranibizumab group. The incidence in the DME studies from baseline to week 52 was 3.3% (19 out of 578) in the combined group of patients treated with aflibercept compared with 2.8% (8 out of 287) in the control group; from baseline to week 100, the incidence was 6.4% (37 out of 578) in the combined group of patients treated with aflibercept compared with 4.2% (12 out of 287) in the control group. There were no reported thromboembolic events in the patients treated with aflibercept in the first six months of the RVO studies.

6. ADVERSE REACTIONS

The following potentially serious adverse reactions are described elsewhere in the labeling:

- Hypersensitivity [see Contraindications (4.3)]
- Endophthalmitis, retinal detachments, and Retinal Vasculitis with or without Occlusion [see Warnings and Precautions (5.1)]
- Increase in intraocular pressure [see Warnings and Precautions (5.2)]
- Thromboembolic events [see Warnings and Precautions (5.4)]

6.1 Clinical Trials Experience

Because clinical trials are conducted under widely varying conditions, adverse reaction rates observed in the clinical trials of a drug cannot be directly compared to rates in other clinical trials of the same or another drug and may not reflect the rates observed in practice.

A total of 2980 adult patients treated with aflibercept constituted the safety population in eight phase 3 studies. Among those, 2379 patients were treated with the recommended dose of 2 mg. Serious adverse reactions related to the injection procedure have occurred in <0.1% of intravitreal injections with aflibercept including endophthalmitis and retinal detachment. The most common adverse reactions (≥5%) reported in patients receiving aflibercept were conjunctival hemorrhage, eye pain, cataract, vitreous detachment, vitreous floaters, and intraocular pressure increased.

Neovascular (Wet) Age-Related Macular Degeneration (AMD)

The data described below reflect exposure to aflibercept in 1824 patients with wet AMD, including 1223 patients treated with the 2-mg dose, in 2 double-masked, controlled clinical studies (VIEW1 and VIEW2) for 24 months (with active control in year 1) [see Clinical Studies (14.1)].

Safety data observed in the aflibercept group in a 52-week, double-masked, Phase 2 study were consistent with these results.

Table 1. Most Common Adverse Reactions (≥1%) in Wet AMD Studies
Adverse Reactions | Baseline to Week 52 |  | Baseline to Week 96
 | Aflibercept (N=1824) | Active Control (ranibizumab) (N=595) | Aflibercept (N=1824) | Control (ranibizumab) (N=595)
Conjunctival hemorrhage | 25% | 28% | 27% | 30%
Eye pain | 9% | 9% | 10% | 10%
Cataract | 7% | 7% | 13% | 10%
Vitreous detachment | 6% | 6% | 8% | 8%
Vitreous floaters | 6% | 7% | 8% | 10%
Intraocular pressure increased | 5% | 7% | 7% | 11%
Ocular hyperemia | 4% | 8% | 5% | 10%
Corneal epithelium defect | 4% | 5% | 5% | 6%
Detachment of the retinal pigment epithelium | 3% | 3% | 5% | 5%
Injection site pain | 3% | 3% | 3% | 4%
Foreign body sensation in eyes | 3% | 4% | 4% | 4%
Lacrimation increased | 3% | 1% | 4% | 2%
Vision blurred | 2% | 2% | 4% | 3%
Intraocular inflammation | 2% | 3% | 3% | 4%
Retinal pigment epithelium tear | 2% | 1% | 2% | 2%
Injection site hemorrhage | 1% | 2% | 2% | 2%
Eyelid edema | 1% | 2% | 2% | 3%
Corneal edema | 1% | 1% | 1% | 1%
Retinal detachment | <1% | <1% | 1% | 1%

Less common serious adverse reactions reported in <1% of the patients treated with aflibercept were hypersensitivity, retinal tear, and endophthalmitis.

Macular Edema Following Retinal Vein Occlusion (RVO)

The data described below reflect 6 months exposure to aflibercept with a monthly 2 mg dose in 218 patients following central retinal vein occlusion (CRVO) in 2 clinical studies (COPERNICUS and GALILEO) and 91 patients following branch retinal vein occlusion (BRVO) in one clinical study (VIBRANT) [see Clinical Studies (14.2), (14.3)].

Table 2. Most Common Adverse Reactions (≥1%) in RVO Studies
Adverse Reactions | CRVO |  | BRVO
 | Aflibercept (N=218) | Control (N=142) | Aflibercept (N=91) | Control (N=92)
Eye pain | 13% | 5% | 4% | 5%
Conjunctival hemorrhage | 12% | 11% | 20% | 4%
Intraocular pressure increased | 8% | 6% | 2% | 0%
Corneal epithelium defect | 5% | 4% | 2% | 0%
Vitreous floaters | 5% | 1% | 1% | 0%
Ocular hyperemia | 5% | 3% | 2% | 2%
Foreign body sensation in eyes | 3% | 5% | 3% | 0%
Vitreous detachment | 3% | 4% | 2% | 0%
Lacrimation increased | 3% | 4% | 3% | 0%
Injection site pain | 3% | 1% | 1% | 0%
Vision blurred | 1% | <1% | 1% | 1%
Intraocular inflammation | 1% | 1% | 0% | 0%
Cataract | <1% | 1% | 5% | 0%
Eyelid edema | <1% | 1% | 1% | 0%

Less common adverse reactions reported in <1% of the patients treated with aflibercept in the CRVO studies were corneal edema, retinal tear, hypersensitivity, and endophthalmitis.

Diabetic Macular Edema (DME) and Diabetic Retinopathy (DR)

The data described below reflect exposure to aflibercept in 578 patients with DME treated with the 2-mg dose in 2 double-masked, controlled clinical studies (VIVID and VISTA) from baseline to week 52 and from baseline to week 100 [see Clinical Studies (14.4)].

Table 3. Most Common Adverse Reactions (≥1%) in DME Studies
Adverse Reactions | Baseline to Week 52 |  | Baseline to Week 100
 | Aflibercept (N=578) | Control (N=287) | Aflibercept (N=578) | Control (N=287)
Conjunctival hemorrhage | 28% | 17% | 31% | 21%
Eye pain | 9% | 6% | 11% | 9%
Cataract | 8% | 9% | 19% | 17%
Vitreous floaters | 6% | 3% | 8% | 6%
Corneal epithelium defect | 5% | 3% | 7% | 5%
Intraocular pressure Increased | 5% | 3% | 9% | 5%
Ocular hyperemia | 5% | 6% | 5% | 6%
Vitreous detachment | 3% | 3% | 8% | 6%
Foreign body sensation in eyes | 3% | 3% | 3% | 3%
Lacrimation increased | 3% | 2% | 4% | 2%
Vision blurred | 2% | 2% | 3% | 4%
Intraocular inflammation | 2% | <1% | 3% | 1%
Injection site pain | 2% | <1% | 2% | <1%
Eyelid edema | <1% | 1% | 2% | 1%

Less common adverse reactions reported in <1% of the patients treated with aflibercept were hypersensitivity, retinal detachment, retinal tear, corneal edema, and injection site hemorrhage.

Safety data observed in 269 patients with nonproliferative diabetic retinopathy (NPDR) through week 52 in the PANORAMA trial were consistent with those seen in the phase 3 VIVID and VISTA trials (see Table 3 above).

6.2 Postmarketing Experience

The following adverse reactions have been identified during postapproval use of aflibercept. Because these reactions are reported voluntarily from a population of uncertain size, it is not always possible to reliably estimate their frequency or establish a causal relationship to drug exposure.

Eye disorders: retinal vasculitis and occlusive retinal vasculitis related to intravitreal injection with aflibercept (reported at a rate of 0.6 and 0.2 per 1 million injections, respectively, based on postmarketing experience from November 2011 until November 2023).

8 USE IN SPECIFIC POPULATIONS

8.1 Pregnancy

Risk Summary

Adequate and well-controlled studies with aflibercept have not been conducted in pregnant women. Aflibercept produced adverse embryofetal effects in rabbits, including external, visceral, and skeletal malformations. A fetal No Observed Adverse Effect Level (NOAEL) was not identified. At the lowest dose shown to produce adverse embryofetal effects, systemic exposures (based on AUC for free aflibercept) were approximately 6 times higher than AUC values observed in humans after a single intravitreal treatment at the recommended clinical dose (see Data).

Animal reproduction studies are not always predictive of human response, and it is not known whether aflibercept can cause fetal harm when administered to a pregnant woman. Based on the anti-VEGF mechanism of action for aflibercept [see Clinical Pharmacology (12.1)], treatment with aflibercept may pose a risk to human embryofetal development. PAVBLU should be used during pregnancy only if the potential benefit justifies the potential risk to the fetus.

All pregnancies have a background risk of birth defect, loss, or other adverse outcomes. The background risk of major birth defects and miscarriage for the indicated population is unknown. In the U.S. general population, the estimated background risk of major birth defects and miscarriage in clinically recognized pregnancies is 2-4% and 15-20%, respectively.

Data

Animal Data

In two embryofetal development studies, aflibercept produced adverse embryofetal effects when administered every three days during organogenesis to pregnant rabbits at intravenous doses ≥3 mg per kg, or every six days during organogenesis at subcutaneous doses ≥0.1 mg per kg.

Adverse embryofetal effects included increased incidences of postimplantation loss and fetal malformations, including anasarca, umbilical hernia, diaphragmatic hernia, gastroschisis, cleft palate, ectrodactyly, intestinal atresia, spina bifida, encephalomeningocele, heart and major vessel defects, and skeletal malformations (fused vertebrae, sternebrae, and ribs; supernumerary vertebral arches and ribs; and incomplete ossification). The maternal No Observed Adverse Effect Level (NOAEL) in these studies was 3 mg per kg. Aflibercept produced fetal malformations at all doses assessed in rabbits and the fetal NOAEL was not identified. At the lowest dose shown to produce adverse embryofetal effects in rabbits (0.1 mg per kg), systemic exposure (AUC) of free aflibercept was approximately 6 times higher than systemic exposure (AUC) observed in adult patients after a single intravitreal dose of 2 mg.

8.2 Lactation

Risk Summary

There is no information regarding the presence of aflibercept products in human milk, the effects of the drug on the breastfed infant, or the effects of the drug on milk production/excretion. Because many drugs are excreted in human milk, and because the potential for absorption and harm to infant growth and development exists, PAVBLU is not recommended during breastfeeding.

The developmental and health benefits of breastfeeding should be considered along with the mother's clinical need for PAVBLU and any potential adverse effects on the breastfed child from PAVBLU.

8.3 Females and Males of Reproductive Potential

Contraception

Females of reproductive potential are advised to use effective contraception prior to the initial dose, during treatment, and for at least 3 months after the last intravitreal injection of PAVBLU.

Infertility

There are no data regarding the effects of aflibercept on human fertility. Aflibercept adversely affected female and male reproductive systems in cynomolgus monkeys when administered by intravenous injection at a dose approximately 1500 times higher than the systemic level observed in adult patients with an intravitreal dose of 2 mg. A No Observed Adverse Effect Level (NOAEL) was not identified. These findings were reversible within 20 weeks after cessation of treatment [see Nonclinical Toxicology (13.1)].

8.4 Pediatric Use

A pediatric assessment for PAVBLU demonstrates that PAVBLU is safe and effective for pediatric patients in an indication for which EYLEA (aflibercept) is approved. However, PAVBLU is not approved for such indication due to marketing exclusivity for EYLEA (aflibercept).

8.5 Geriatric Use

In the clinical studies, approximately 76% (2049/2701) of patients randomized to treatment with aflibercept were ≥65 years of age and approximately 46% (1250/2701) were ≥75 years of age. No significant differences in efficacy or safety were seen with increasing age in these studies.

10 OVERDOSAGE

Overdosing with increased injection volume may increase intraocular pressure. Therefore, in case of overdosage, intraocular pressure should be monitored and if deemed necessary by the treating physician, adequate treatment should be initiated.

11 DESCRIPTION

Aflibercept-ayyh is a recombinant fusion protein consisting of portions of human VEGF receptors 1 and 2 extracellular domains fused to the Fc portion of human IgG1 formulated as an iso-osmotic solution for intravitreal administration. Aflibercept-ayyh is a dimeric glycoprotein with a protein molecular weight of 97 kilodaltons (kDa) and contains glycosylation, constituting an additional 15% of the total molecular mass, resulting in a total molecular weight of 115 kDa. Aflibercept-ayyh is produced in recombinant Chinese hamster ovary (CHO) cells.

PAVBLU (aflibercept-ayyh) injection is a sterile, clear to opalescent and colorless to slightly yellow solution. PAVBLU does not contain anti-microbial preservative and is supplied as an aqueous solution for intravitreal injection in a single-dose prefilled plastic syringe or a single-dose glass vial designed to deliver 0.05 mL (50 microliters) of solution containing 2 mg of aflibercept-ayyh in polysorbate 80 (0.005 mg), sucrose (2.5 mg), trehalose (1.58 mg) and water for injection with a pH of 6.2.

12 CLINICAL PHARMACOLOGY

12.1 Mechanism of Action

Vascular endothelial growth factor-A (VEGF-A) and placental growth factor (PlGF) are members of the VEGF family of angiogenic factors that can act as mitogenic, chemotactic, and vascular permeability factors for endothelial cells. VEGF acts via two receptor tyrosine kinases, VEGFR-1 and VEGFR-2, present on the surface of endothelial cells. PlGF binds only to VEGFR-1, which is also present on the surface of leucocytes. Activation of these receptors by VEGF-A can result in neovascularization and vascular permeability.

Aflibercept products act as a soluble decoy receptor that binds VEGF-A and PlGF, and thereby can inhibit the binding and activation of these cognate VEGF receptors.

12.2 Pharmacodynamics

Neovascular (Wet) Age-Related Macular Degeneration (AMD)

In the clinical studies anatomic measures of disease activity improved similarly in all treatment groups from baseline to week 52. Anatomic data were not used to influence treatment decisions during the first year.

Macular Edema Following Retinal Vein Occlusion (RVO)

Reductions in mean retinal thickness were observed in COPERNICUS, GALILEO, and VIBRANT at week 24 compared to baseline. Anatomic data were not used to influence treatment decisions [see Clinical Studies (14.2), (14.3)].

Diabetic Macular Edema (DME)

Reductions in mean retinal thickness were observed in VIVID and VISTA at weeks 52 and 100 compared to baseline. Anatomic data were not used to influence aflibercept treatment decisions [see Clinical Studies (14.4)].

12.3 Pharmacokinetics

Aflibercept is administered intravitreally to exert local effects in the eye. In patients with wet AMD, RVO, or DME, following intravitreal administration of aflibercept, a fraction of the administered dose is expected to bind with endogenous VEGF in the eye to form an inactive aflibercept: VEGF complex. Once absorbed into the systemic circulation, aflibercept presents in the plasma as free aflibercept (unbound to VEGF) and a more predominant stable inactive form with circulating endogenous VEGF (i.e., aflibercept: VEGF complex).

Absorption/Distribution

Following intravitreal administration of 2 mg per eye of aflibercept to patients with wet AMD, RVO, and DME, the mean Cmax of free aflibercept in the plasma was 0.02 mcg/mL (range: 0 to 0.054 mcg/mL), 0.05 mcg/mL (range: 0 to 0.081 mcg/mL), and 0.03 mcg/mL (range: 0 to 0.076 mcg/mL), respectively and was attained in 1 to 3 days. The free aflibercept plasma concentrations were undetectable two weeks post-dosing in all patients. Aflibercept did not accumulate in plasma when administered as repeated doses intravitreally every 4 weeks. It is estimated that after intravitreal administration of 2 mg to patients, the mean maximum plasma concentration of free aflibercept is more than 100 fold lower than the concentration of aflibercept required to half-maximally bind systemic VEGF.

The volume of distribution of free aflibercept following intravenous (I.V.) administration of aflibercept has been determined to be approximately 6 L.

Metabolism/Elimination

Aflibercept is a therapeutic protein and no drug metabolism studies have been conducted. Aflibercept is expected to undergo elimination through both target-mediated disposition via binding to free endogenous VEGF and metabolism via proteolysis. The terminal elimination half-life (t1/2) of free aflibercept in plasma was approximately 5 to 6 days after I.V. administration of doses of 2 to 4 mg/kg aflibercept.

Specific Populations

Renal Impairment

Pharmacokinetic analysis of a subgroup of patients (n=492) in one wet AMD study, of which 43% had renal impairment (mild n=120, moderate n=74, and severe n=16), revealed no differences with respect to plasma concentrations of free aflibercept after intravitreal administration every 4 or 8 weeks. Similar results were seen in patients in a RVO study and in patients in a DME study. No dose adjustment based on renal impairment status is needed for either wet AMD, RVO, or DME patients.

Other

No dosage modification is required based on gender or in the elderly.

12.6 Immunogenicity

The observed incidence of anti-drug antibodies is highly dependent on the sensitivity and specificity of the assay. Differences in assay methods preclude meaningful comparisons of the incidence of anti-drug antibodies in the studies described below with the incidence of anti-drug antibodies in other studies, including those of aflibercept or of other aflibercept products.

In the wet AMD, RVO, and DME studies, the pre-treatment incidence of immunoreactivity to aflibercept was approximately 1% to 3% across treatment groups. After dosing with aflibercept for 24-100 weeks, antibodies to aflibercept were detected in a similar percentage range of patients.

There were no differences in efficacy or safety between patients with or without immunoreactivity.

13 NONCLINICAL TOXICOLOGY

13.1 Carcinogenesis, Mutagenesis, Impairment of Fertility

No studies have been conducted on the mutagenic or carcinogenic potential of aflibercept products. Effects on male and female fertility were assessed as part of a 6-month study in monkeys with intravenous administration of aflibercept at weekly doses ranging from 3 to 30 mg per kg. Absent or irregular menses associated with alterations in female reproductive hormone levels and changes in sperm morphology and motility were observed at all dose levels. In addition, females showed decreased ovarian and uterine weight accompanied by compromised luteal development and reduction of maturing follicles. These changes correlated with uterine and vaginal atrophy. A No Observed Adverse Effect Level (NOAEL) was not identified. Intravenous administration of the lowest dose of aflibercept assessed in monkeys (3 mg per kg) resulted in systemic exposure (AUC) for free aflibercept that was approximately 1500 times higher than the systemic exposure observed in adult patients after an intravitreal dose of 2 mg. All changes were reversible within 20 weeks after cessation of treatment.

13.2 Animal Toxicology and/or Pharmacology

Erosions and ulcerations of the respiratory epithelium in nasal turbinates in monkeys treated with aflibercept intravitreally were observed at intravitreal doses of 2 or 4 mg per eye. At the NOAEL of 0.5 mg per eye in monkeys, the systemic exposure (AUC) was 56 times higher than the exposure observed in adult patients after an intravitreal dose of 2 mg. Similar effects were not seen in other clinical studies [see Clinical Studies (14)].

14 CLINICAL STUDIES

14.1 Neovascular (Wet) Age-Related Macular Degeneration (AMD)

The safety and efficacy of aflibercept were assessed in two randomized, multi-center, double-masked, active-controlled studies in patients with wet AMD. A total of 2412 patients were treated and evaluable for efficacy (1817 with aflibercept) in the two studies (VIEW1 and VIEW2). In each study, up to week 52, patients were randomly assigned in a 1:1:1:1 ratio to 1 of 4 dosing regimens: 1) aflibercept administered 2 mg every 8 weeks following 3 initial monthly doses (aflibercept 2Q8); 2) aflibercept administered 2 mg every 4 weeks (aflibercept 2Q4); 3) aflibercept 0.5 mg administered every 4 weeks (aflibercept 0.5Q4); and 4) ranibizumab administered 0.5 mg every 4 weeks (ranibizumab 0.5 mg Q4). Protocol-specified visits occurred every 28±3 days. Patient ages ranged from 49 to 99 years with a mean of 76 years.

In both studies, the primary efficacy endpoint was the proportion of patients who maintained vision, defined as losing fewer than 15 letters of visual acuity at week 52 compared to baseline. Both aflibercept 2Q8 and aflibercept 2Q4 groups were shown to have efficacy that was clinically equivalent to the ranibizumab 0.5 mg Q4 group in year 1.

Detailed results from the analysis of the VIEW1 and VIEW2 studies are shown in Table 4 and Figure 13 below.

Table 4. Efficacy Outcomes at Week 52 (Full Analysis Set with LOCF) in VIEW1 and VIEW2 Studies
 | VIEW 1 |  |  | VIEW 2
 | Aflibercept 2 mg Q8 weeks [After treatment initiation with 3 monthly doses] | Aflibercept 2 mg Q4 weeks | Ranibizumab 0.5 mg Q4 weeks | Aflibercept 2 mg Q8 weeks | Aflibercept 2 mg Q4 weeks | Ranibizumab 0.5 mg Q4 weeks
Full Analysis Set | N=301 | N=304 | N=304 | N=306 | N=309 | N=291
Efficacy Outcomes
Proportion of patients who maintained visual acuity (%) (<15 letters of BCVA loss) | 94% | 95% | 94% | 95% | 95% | 95%
Difference [Aflibercept group minus the ranibizumab group] (%) (95.1% CI) | 0.6 (-3.2, 4.4) | 1.3 (-2.4, 5.0) |  | 0.6 (-2.9, 4.0) | -0.3 (-4.0, 3.3)
Mean change in BCVA as measured by ETDRS letter score from Baseline | 7.9 | 10.9 | 8.1 | 8.9 | 7.6 | 9.4
Difference in LS mean (95.1% CI) | 0.3 (-2.0, 2.5) | 3.2 (0.9, 5.4) |  | -0.9 (-3.1, 1.3) | -2.0 (-4.1, 0.2)
Number of patients who gained at least 15 letters of vision from Baseline (%) | 92 (31%) | 114 (38%) | 94 (31%) | 96 (31%) | 91 (29%) | 99 (34%)
Difference (%) (95.1% CI) | -0.4 (-7.7, 7.0) | 6.6 (-1.0, 14.1) |  | -2.6 (-10.2, 4.9) | -4.6 (-12.1, 2.9)
BCVA = Best Corrected Visual Acuity; CI = Confidence Interval; ETDRS = Early Treatment Diabetic Retinopathy Study; LOCF = Last Observation Carried Forward (baseline values are not carried forward); 95.1% confidence intervals were presented to adjust for safety assessment conducted during the study

Treatment effects in evaluable subgroups (e.g., age, gender, race, baseline visual acuity) in each study were in general consistent with the results in the overall populations.

Figure 13. Mean Change in Visual Acuity from Baseline to Week 96 [Patient dosing schedules were individualized from weeks 52 to 96 using a modified 12-week dosing regimen.] in VIEW1 and VIEW2 Studies

VIEW1 and VIEW2 studies were both 96 weeks in duration. However after 52 weeks patients no longer followed a fixed dosing schedule. Between week 52 and week 96, patients continued to receive the drug and dosage strength to which they were initially randomized on a modified 12 week dosing schedule (doses at least every 12 weeks and additional doses as needed). Therefore, during the second year of these studies there was no active control comparison arm.

14.2 Macular Edema Following Central Retinal Vein Occlusion (CRVO)

The safety and efficacy of aflibercept were assessed in two randomized, multi-center, double-masked, sham-controlled studies in patients with macular edema following CRVO. A total of 358 patients were treated and evaluable for efficacy (217 with aflibercept) in the two studies (COPERNICUS and GALILEO). In both studies, patients were randomly assigned in a 3:2 ratio to either 2 mg aflibercept administered every 4 weeks (2Q4), or sham injections (control group) administered every 4 weeks for a total of 6 injections. Protocol-specified visits occurred every 28±7 days. Patient ages ranged from 22 to 89 years with a mean of 64 years.

In both studies, the primary efficacy endpoint was the proportion of patients who gained at least 15 letters in BCVA compared to baseline. At week 24, the aflibercept 2 mg Q4 group was superior to the control group for the primary endpoint.

Results from the analysis of the COPERNICUS and GALILEO studies are shown in Table 5 and Figure 14 below.

Table 5. Efficacy Outcomes at Week 24 (Full Analysis Set with LOCF) in COPERNICUS and GALILEO Studies
 | COPERNICUS |  | GALILEO
 | Control | Aflibercept 2 mg Q4 weeks | Control | Aflibercept 2 mg Q4 weeks
 | N=73 | N=114 | N=68 | N=103
Efficacy Outcomes
Proportion of patients who gained at least 15 letters in BCVA from Baseline (%) | 12% | 56% | 22% | 60%
Weighted Difference [Difference is aflibercept 2 mg Q4 weeks minus Control] , [Difference and CI are calculated using Cochran-Mantel-Haenszel (CMH) test adjusted for baseline factors; 95.1% confidence intervals were presented to adjust for the multiple assessments conducted during the study] (%) |  | 44.8% [p<0.01 compared with Control] |  | 38.3%
(95.1% CI) |  | (32.9, 56.6) |  | (24.4, 52.1)
Mean change in BCVA as measured by ETDRS letter score from Baseline (SD) | -4.0 | 17.3 | 3.3 | 18.0
Mean change in BCVA as measured by ETDRS letter score from Baseline (SD) | (18.0) | (12.8) | (14.1) | (12.2)
Difference in LS mean, [LS mean and CI based on an ANCOVA model] |  | 21.7 |  | 14.7
(95.1% CI) |  | (17.3, 26.1) |  | (10.7, 18.7)

Figure 14. Mean Change in BCVA as Measured by ETDRS Letter Score from Baseline to Week 24 in COPERNICUS and GALILEO Studies

Treatment effects in evaluable subgroups (e.g., age, gender, race, baseline visual acuity, retinal perfusion status, and CRVO duration) in each study and in the combined analysis were in general consistent with the results in the overall populations.

14.3 Macular Edema Following Branch Retinal Vein Occlusion (BRVO)

The safety and efficacy of aflibercept were assessed in a 24-week, randomized, multi-center, double-masked, controlled study in patients with macular edema following BRVO. A total of 181 patients were treated and evaluable for efficacy (91 with aflibercept) in the VIBRANT study. In the study, patients were randomly assigned in a 1:1 ratio to either 2 mg aflibercept administered every 4 weeks (2Q4) or laser photocoagulation administered at baseline and subsequently as needed (control group). Protocol-specified visits occurred every 28±7 days. Patient ages ranged from 42 to 94 years with a mean of 65 years.

In the VIBRANT study, the primary efficacy endpoint was the proportion of patients who gained at least 15 letters in BCVA at week 24 compared to baseline. At week 24, the aflibercept 2 mg Q4 group was superior to the control group for the primary endpoint.

Detailed results from the analysis of the VIBRANT study are shown in Table 6 and Figure 15 below.

Table 6. Efficacy Outcomes at Week 24 (Full Analysis Set with LOCF) in VIBRANT Study
 | VIBRANT
 | Control | Aflibercept 2 mg Q4 weeks
 | N=90 | N=91
Efficacy Outcomes
Proportion of patients who gained at least 15 letters in BCVA from Baseline (%) | 26.7% | 52.7%
Weighted Difference [Difference is aflibercept 2 mg Q4 weeks minus Control] , [Difference and CI are calculated using Mantel-Haenszel weighting scheme adjusted for region (North America vs. Japan) and baseline BCVA category (> 20/200 and ≤ 20/200)] (%) |  | 26.6% [p<0.01 compared with Control]
(95% CI) |  | (13.0, 40.1)
Mean change in BCVA as measured by ETDRS letter score from Baseline (SD) | 6.9 | 17.0
Mean change in BCVA as measured by ETDRS letter score from Baseline (SD) | (12.9) | (11.9)
Difference in LS mean, [LS mean and CI based on an ANCOVA model] |  | 10.5
(95.1% CI) |  | (7.1, 14.0)

Figure 15. Mean Change in BCVA as Measured by ETDRS Letter Score from Baseline to Week 24 in VIBRANT Study

Treatment effects in evaluable subgroups (e.g., age, gender, and baseline retinal perfusion status) in the study were in general consistent with the results in the overall populations.

14.4 Diabetic Macular Edema (DME)

The safety and efficacy of aflibercept were assessed in two randomized, multi-center, double-masked, controlled studies in patients with DME. A total of 862 randomized and treated patients were evaluable for efficacy. Protocol-specified visits occurred every 28±7 days. Patient ages ranged from 23 to 87 years with a mean of 63 years.

Of those, 576 were randomized to aflibercept groups in the two studies (VIVID and VISTA). In each study, patients were randomly assigned in a 1:1:1 ratio to 1 of 3 dosing regimens: 1) aflibercept administered 2 mg every 8 weeks following 5 initial monthly injections (aflibercept 2Q8); 2) aflibercept administered 2 mg every 4 weeks (aflibercept 2Q4); and 3) macular laser photocoagulation (at baseline and then as needed). Beginning at week 24, patients meeting a pre-specified threshold of vision loss were eligible to receive additional treatment: patients in the aflibercept groups could receive laser and patients in the laser group could receive aflibercept.

In both studies, the primary efficacy endpoint was the mean change from baseline in BCVA at week 52 as measured by ETDRS letter score. Efficacy of both aflibercept 2Q8 and aflibercept 2Q4 groups was statistically superior to the control group. This statistically superior improvement in BCVA was maintained at week 100 in both studies.

Results from the analysis of the VIVID and VISTA studies are shown in Table 7 and Figure 16 below.

Table 7. Efficacy Outcomes at Weeks 52 and 100 (Full Analysis Set with LOCF) in VIVID and VISTA Studies
 | VIVID |  |  | VISTA
 | Aflibercept 2 mg Q8 weeks [After treatment initiation with 5 monthly injections] | Aflibercept 2 mg Q4 weeks | Control | Aflibercept 2 mg Q8 weeks | Aflibercept 2 mg Q4 weeks | Control
Full Analysis Set | N=135 | N=136 | N=132 | N=151 | N=154 | N=154
Efficacy Outcomes at Week 52
Mean change in BCVA as measured by ETDRS letter score from Baseline (SD) | 10.7 | 10.5 | 1.2 | 10.7 | 12.5 | 0.2
Mean change in BCVA as measured by ETDRS letter score from Baseline (SD) | (9.3) | (9.6) | (10.6) | (8.2) | (9.5) | (12.5)
Difference [LS mean and CI based on an ANCOVA model with baseline BCVA measurement as a covariate and a factor for treatment group. Additionally, protocol specified stratification factors were included in the model.] , [Difference is aflibercept group minus Control group] in LS mean | 9.1 [p<0.01 compared with Control] | 9.3 |  | 10.5 | 12.2
(97.5% CI) | (6.3, 11.8) | (6.5, 12.0) |  | (7.7, 13.2) | (9.4, 15.0)
Proportion of patients who gained at least 15 letters in BCVA from Baseline (%) | 33.3% | 32.4% | 9.1% | 31.1% | 41.6% | 7.8%
Adjusted Difference, [Difference with confidence interval (CI) and statistical test is calculated using Mantel-Haenszel weighting scheme adjusted by protocol specified stratification factors] (%) | 24.2% | 23.3% |  | 23.3% | 34.2%
(97.5% CI) | (13.5, 34.9) | (12.6, 33.9) |  | (13.5, 33.1) | (24.1, 44.4)
Efficacy Outcomes at Week 100
Mean change in BCVA as measured by ETDRS letter score from Baseline (SD) | 9.4 | 11.4 | 0.7 | 11.1 | 11.5 | 0.9
Mean change in BCVA as measured by ETDRS letter score from Baseline (SD) | (10.5) | (11.2) | (11.8) | (10.7) | (13.8) | (13.9)
Difference, in LS mean | 8.2 | 10.7 |  | 10.1 | 10.6
(97.5% CI) | (5.2, 11.3) | (7.6, 13.8) |  | (7.0, 13.3) | (7.1, 14.2)
Proportion of patients who gained at least 15 letters in BCVA from Baseline (%) | 31.1% | 38.2% | 12.1% | 33.1% | 38.3% | 13.0%
Adjusted Difference, (%) | 19.0% | 26.1% |  | 20.1% | 25.8%
(97.5% CI) | (8.0, 29.9) | (14.8, 37.5) |  | (9.6, 30.6) | (15.1, 36.6)

Figure 16. Mean Change in BCVA as Measured by ETDRS Letter Score from Baseline to Week 100 in VIVID and VISTA Studies

Treatment effects in the subgroup of patients who had previously been treated with a VEGF inhibitor prior to study participation were similar to those seen in patients who were VEGF inhibitor naïve prior to study participation.

Treatment effects in evaluable subgroups (e.g., age, gender, race, baseline HbA1c, baseline visual acuity, prior anti-VEGF therapy) in each study were in general consistent with the results in the overall populations.

14.5 Diabetic Retinopathy (DR)

Efficacy and safety data of aflibercept in diabetic retinopathy (DR) are derived from the VIVID, VISTA, and PANORAMA studies.

VIVID AND VISTA

In the VIVID and VISTA studies, an efficacy outcome was the change in the Early Treatment Diabetic Retinopathy Study (ETDRS) Diabetic Retinopathy Severity Scale (ETDRS-DRSS). The ETDRS-DRSS score was assessed at baseline and approximately every 6 months thereafter for the duration of the studies [see Clinical Studies (14.4)].

All enrolled patients had DR and DME at baseline. The majority of patients enrolled in these studies (77%) had moderate-to-severe nonproliferative diabetic retinopathy (NPDR) based on the ETDRS-DRSS. At week 100, the proportion of patients improving by at least 2 steps on the ETDRS-DRSS was significantly greater in both aflibercept treatment groups (2Q4 and 2Q8) when compared to the control group.

Results from the analysis of ETDRS-DRSS at week 100 in the VIVID and VISTA studies are shown in Table 8 below.

Table 8. Proportion of Patients Who Achieved a ≥2-Step Improvement from Baseline in the ETDRS-DRSS Score at Week 100 in VIVID and VISTA Studies
 | VIVID |  |  | VISTA
 | Aflibercept 2 mg Q8 weeks [After treatment initiation with 5 monthly injections] | Aflibercept 2 mg Q4 weeks | Control | Aflibercept 2 mg Q8 weeks | Aflibercept 2 mg Q4 weeks | Control
Evaluable Patients [The number of evaluable patients included all patients who had valid ETDRS-DRSS data at baseline] | N=101 | N=97 | N=99 | N=148 | N=153 | N=150
Number of patients with a ≥2-step improvement on ETDRS-DRSS from Baseline (%) | 32 | 27 | 7 | 56 | 58 | 24
Number of patients with a ≥2-step improvement on ETDRS-DRSS from Baseline (%) | (32%) | (28%) | (7%) | (38%) | (38%) | (16%)
Difference [Difference with confidence interval (CI) was calculated using Mantel-Haenszel weighting scheme adjusted by protocol specified stratification factors] , [Difference is aflibercept minus Control group] (%) (97.5% CI) | 24% [p<0.01 compared with Control] (12, 36) | 21% (9, 33) |  | 22% (11, 33) | 22% (11, 33)
Non-gradable post-baseline ETDRS-DRSS values were treated as missing and were imputed using the last gradable ETDRS-DRSS values (including baseline values if all post-baseline values were missing or non-gradable)

Results of the evaluable subgroups (e.g., age, gender, race, baseline HbA1c, baseline visual acuity) on the proportion of patients who achieved a ≥2-step improvement on the ETDRS-DRSS from baseline to week 100 were, in general, consistent with those in the overall population.

PANORAMA

The PANORAMA study assessed the safety and efficacy of aflibercept in a randomized, multi-center, double-masked, controlled study in patients with moderately severe to severe nonproliferative diabetic retinopathy (NPDR) (ETDRS-DRSS of 47 or 53), without central-involved DME (CI-DME). A total of 402 randomized patients were evaluable for efficacy. Protocol-specified visits occurred every 28±7 days for the first 5 visits, then every 8 weeks (56±7 days). Patient ages ranged from 25 to 85 years with a mean of 55.7 years.

Patients were randomly assigned in a 1:1:1 ratio to 1 of 3 dosing regimens: 1) 3 initial monthly aflibercept 2 mg injections followed by one injection after 8 weeks and then one injection every 16 weeks (aflibercept 2Q16); 2) 5 monthly aflibercept 2 mg injections followed by one injection every 8 weeks (aflibercept 2Q8); and 3) sham treatment.

The primary efficacy endpoint was the proportion of patients who improved by ≥2 steps on the DRSS from baseline to week 24 in the combined aflibercept groups and at week 52 in the 2Q16 and 2Q8 groups individually versus sham. A key secondary endpoint was the proportion of patients developing the composite endpoint of proliferative diabetic retinopathy or anterior segment neovascularization through week 52.

At week 52, efficacy in the 2Q16 and 2Q8 groups was superior to the sham group (see Table 9 and Table 10). The proportion of patients with a ≥2-step improvement over time is shown in Figure 17.

Table 9. Proportion of Patients Who Achieved a ≥2-Step Improvement from Baseline in the ETDRS-DRSS Score at Weeks 24 and 52 in PANORAMA
 | PANORAMA
 | Week 24 |  | Week 52
 | Aflibercept Combined | Control (sham) | Aflibercept 2Q16 | Aflibercept 2Q8 | Control (sham)
Full Analysis Set | N=269 | N=133 | N=135 | N=134 | N=133
Proportion of patients with a ≥2-step improvement on ETDRS-DRSS from Baseline (%) | 58% | 6% | 65% | 80% | 15%
Adjusted Difference [Difference is aflibercept group minus sham] (%) | 52% [p<0.01 compared with Control. p-value was calculated using a 2-sided Cochran-Mantel-Haenszel test adjusted by baseline DRSS stratification variable.] |  | 50% | 65%
(95% CI) [Difference with CI was calculated using the Mantel-Haenszel weighting scheme adjusted by baseline DRSS stratification variable] | (45, 60) |  | (40, 60) | (56, 74)
Non-gradable post-baseline ETDRS-DRSS values were treated as missing and were imputed using the last gradable ETDRS-DRSS values (including baseline values if all post-baseline values were missing or non-gradable)

Figure 17. Proportion of Patients Who Achieved a ≥2-Step Improvement from Baseline in the ETDRS-DRSS Score Through Week 52 in PANORAMA

Table 10. Effect of Aflibercept on Worsening of Diabetic Retinopathy in PANORAMA through Week 52
 | Aflibercept 2Q16 | Aflibercept 2Q8 | Control (sham)
Full Analysis Set | N=135 | N=134 | N=133
Composite Endpoint of Developing PDR or ASNV [As diagnosed by either the Reading Center or Investigator through week 52]
Event Rate [Estimated using Kaplan-Meier method] | 4.0% [p<0.01 compared with Control] | 2.4% | 20.1%
Hazard Ratio | 0.15 | 0.12
Development of Proliferative Diabetic Retinopathy [Defined as ≥2-step worsening on the ETDRS-DRSS score through week 52]
Event Rate | 1.6% | 0.0% | 11.9%
Hazard Ratio | 0.11 | 0.00
PDR = Proliferative Diabetic Retinopathy; ASNV = Anterior Segment Neovascularization

16 HOW SUPPLIED/STORAGE AND HANDLING

16.1 How Supplied

Each prefilled syringe or vial is for single eye use only. Discard unused portion. PAVBLU injection is a clear to opalescent and colorless to slightly yellow solution supplied in the following presentations:

NDC NUMBER | CARTON TYPE | CARTON CONTENTS
55513-056-01 | Prefilled Syringe | one blister pack containing one PAVBLU 2 mg (0.05 mL of a 40 mg/mL solution) sterile, single-dose prefilled plastic syringe one Prescribing Information
55513-065-01 | Vial Only | one PAVBLU 2 mg (0.05 mL of a 40 mg/mL solution) single-dose glass vial one Prescribing Information

16.2 Storage and Handling

Refrigerate PAVBLU at 2°C to 8ºC (36°F to 46ºF). PAVBLU may be kept at room temperature (up to 30° C (86° F)) for a single-period of 3 days. Do not freeze. Do not use beyond the date stamped on the carton and container label. Store in the original carton until time of use to protect from light. Do not open sealed blister tray until time of use.

17 PATIENT COUNSELING INFORMATION

In the days following PAVBLU administration, patients are at risk of developing endophthalmitis, retinal detachment, or retinal vasculitis with or without occlusion. If the eye becomes red, sensitive to light, painful, or develops a change in vision, advise patients and/or caregivers to seek immediate care from an ophthalmologist [see Warnings and Precautions (5.1)].

Patients may experience temporary visual disturbances after an intravitreal injection with PAVBLU and the associated eye examinations [see Adverse Reactions (6)]. Advise patients not to drive or use machinery until visual function has recovered sufficiently.

PAVBLU™ (aflibercept-ayyh)

Manufactured by:
Amgen, Inc.
One Amgen Center Drive
Thousand Oaks, CA 91320-1799

U.S. License Number 1080

AMGEN® and PAVBLU™ (aflibercept-ayyh) are trademarks owned or licensed by Amgen, Inc., its subsidiaries, or affiliates. EYLEA® (aflibercept) is a trademark owned or licensed by Regeneron Pharmaceuticals Inc., its subsidiaries, or affiliates.

© 2024 Amgen, Inc. All rights reserved.

1xxxxxx-v1

PRINCIPAL DISPLAY PANEL - 0.05 mL Syringe Carton

2 mg /
0.05 mL

AMGEN®

PAVBLU™
(aflibercept-ayyh)
Injection

NDC 55513-056-01

2 mg (0.05 mL of 40 mg/mL solution)

Carton contents: one blister pack containing one sterile, single-dose prefilled plastic
syringe and package insert.

Prefilled syringe contents:
Each PAVBLU™ single-dose prefilled syringe is designed to deliver 2 mg of aflibercept-ayyh
in 0.05 mL (50 microliters) solution with polysorbate 80 (0.005 mg), sucrose (2.5 mg),
trehalose (1.58 mg) and water for injection with a pH of 6.2.

Recommended Dosage: See prescribing information.

Rx Only

PRINCIPAL DISPLAY PANEL - 0.05 mL Vial Carton

2 mg /
0.05 mL

NDC 55513-065-01

PAVBLU™
(aflibercept-ayyh)
Injection

2 mg (0.05 mL of
40 mg/mL solution)

For Intravitreal Injection
One Single-Dose Vial

Sterile Solution
Contains no anti-microbial
preservatives.
Keep out of reach of children
Discard unused portion

AMGEN®
Rx Only